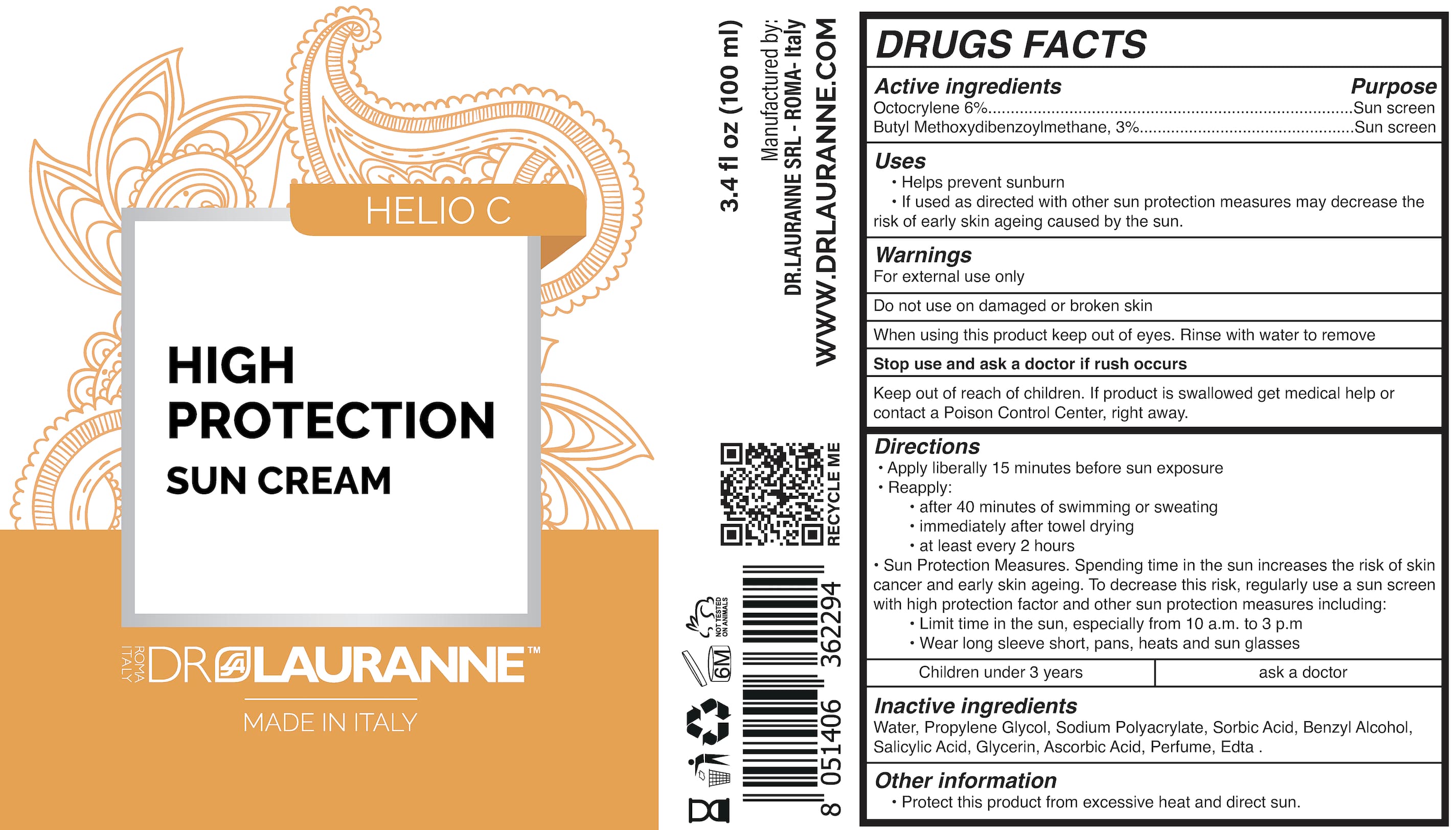 DRUG LABEL: DR LAURANNE
NDC: 84127-111 | Form: CREAM
Manufacturer: DR LAURANNE SRL
Category: otc | Type: HUMAN OTC DRUG LABEL
Date: 20241225

ACTIVE INGREDIENTS: AVOBENZONE 3 g/100 mL; OCTOCRYLENE 6 g/100 mL
INACTIVE INGREDIENTS: PROPYLENE GLYCOL; SODIUM POLYACRYLATE (2500000 MW); EDETIC ACID; ASCORBIC ACID; GLYCERIN; WATER; BENZYL ALCOHOL; SORBIC ACID; SALICYLIC ACID

DR. LAURANNE SUNSCREEN

Active Ingredient

Octocrylene 6%...Sun screen

Butyl Methoxydibenzoylmethane, 3%....Sun screen

Use

sunscreen

INDICATIONS AND USAGE

Helps prevent sunburn
If used as directed with other sun protection measures may decrease the risk of early skin ageing caused by the sun.

Warnings

For external use only

Do not use on damaged or broken skin

When using this product keep out of eyes. Rinse with water to remove

Stop use and ask a doctor if rush occurs

Directions

Apply liberally 15 minutes before sun exposure

Reapply:
After 40 minutes of swimming or sweating immediately after towel drying at least every 2 hours
Sun Protection Measures. Spending sun exposure increases the risk of skin cancer and early skin ageing. To decrease this risk, regularly use sunscreen with high protection factors and other sun protection measures including:
Limit time in the sun, especially from 10 a.m. to 3 p.m Wear long sleeve short, pans, heats and sun glasses

Children under 3 vears ask a doctor

Other information

Protect this product from excessive heat and direct sun.

Inactive ingredients

Water, Propylene Glycol, Sodium Polyacrylate, Sorbic Acid, Benzyl Alcohol, Salicylic Acid, Glycerin, Ascorbic Acid, Perfume, Edta.

KEEP OUT OF REACH OF CHILDREN

If product is swallowed get medical help or contact a Poison Control Center, right away.

PACKAGE LABEL

100 mL NDC: 84127-111-11